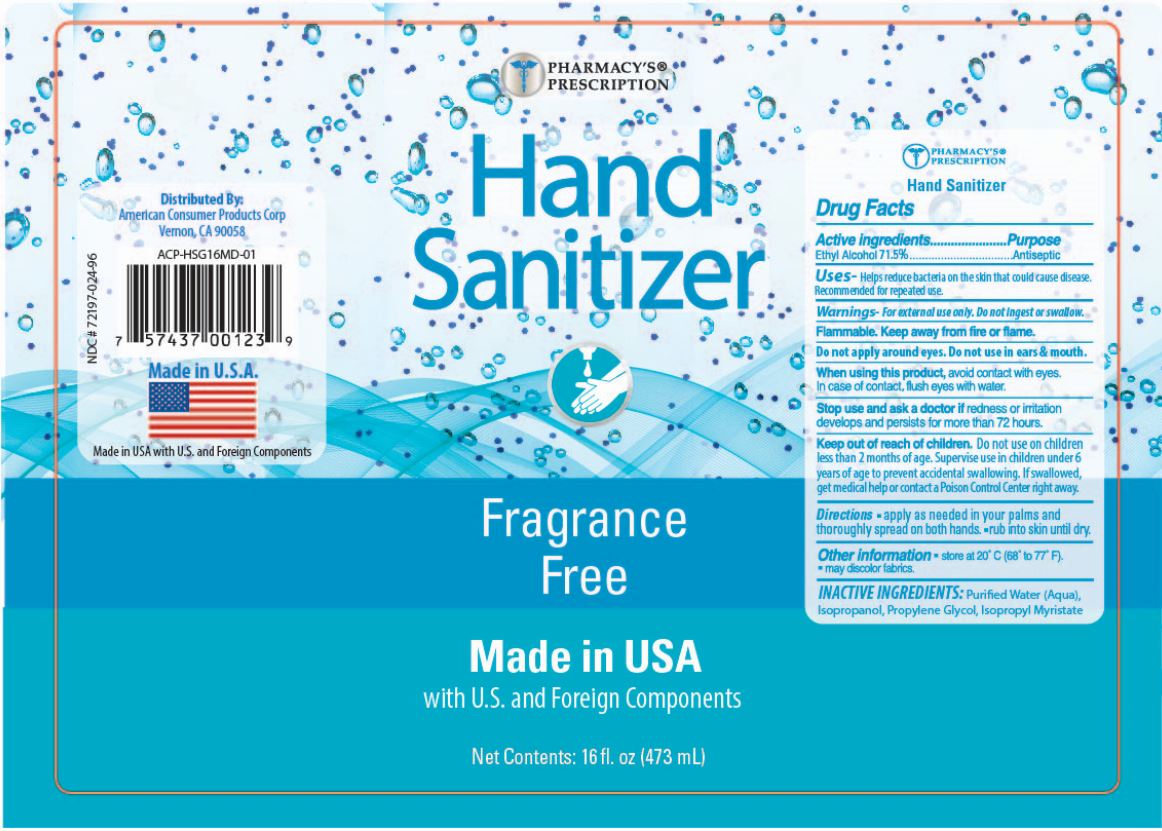 DRUG LABEL: Pharmacys Prescription Hand Sanitizer
NDC: 72197-024 | Form: GEL
Manufacturer: American Consumer Products Corp
Category: otc | Type: HUMAN OTC DRUG LABEL
Date: 20200428

ACTIVE INGREDIENTS: ALCOHOL 71.5 mL/100 mL
INACTIVE INGREDIENTS: ISOPROPYL ALCOHOL; PROPYLENE GLYCOL; ISOPROPYL MYRISTATE; WATER

Pharmacys Prescription Hand Sanitizer

Active Ingredients

Active ingredients - Ethyl Alcool 71.5%

Purpose

Purpose - Antiseptic

Warnings

Warnings - For external use only. Do not ingest or swallow.

Flammable. Keep away from fire or flame.

Do not apply around eyes. Do not use in ears & mouth.

Indications & Usage

When using this product, avoid contact with eyes. In case of contact, flush eyes with water.

Stop Use

Stop use and ask a doctor if redness or irritation develps and persists for more than 72 hours.

Keep out of reach of children. Do not use on children less than 2 months of age. Supervise use in children under 6 years of age to prevent accidental swallowing. If swallowed, get medical help or contact a Poison Control Center right away.

Directions

Directions - Apply as needed into your palms and thoroughly spread on both hands - rub in skin until dry.

Other Information

Other information - store at 20°C (68° to 77° F).

-may discolor fabrics.

Inactive Ingredients

INACTIVE INGREDIENTS: Purified Water (Aqua), Isopropanol, Propylene Glycol, Isopropyl Myristate

Distributed By:

American Consumer Products Corp

Vernon, CA 90058